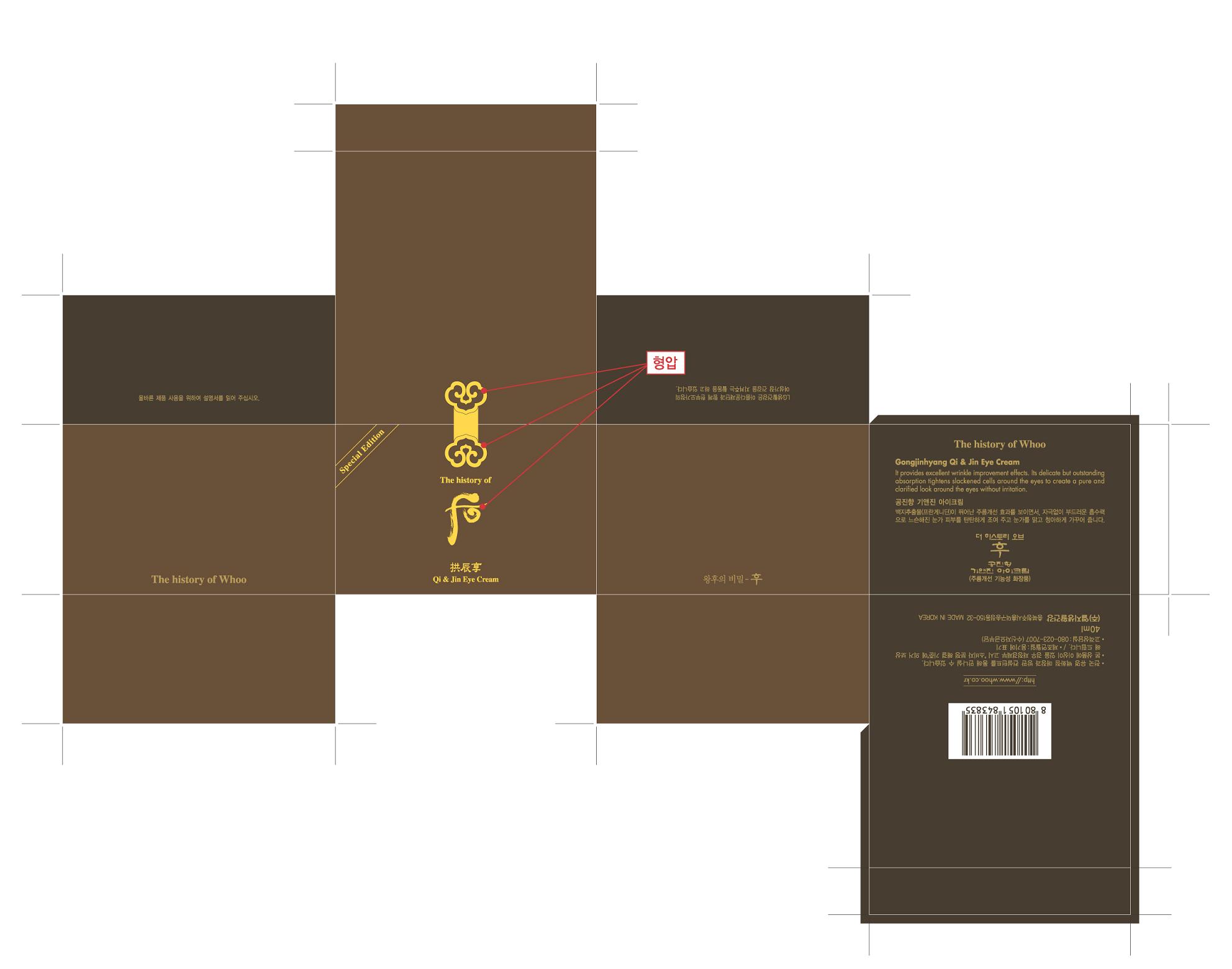 DRUG LABEL: Gongjinhyang Qi and Jin Eye 
NDC: 53208-460 | Form: CREAM
Manufacturer: LG Household and Healthcare, Inc.
Category: otc | Type: HUMAN OTC DRUG LABEL
Date: 20100608

ACTIVE INGREDIENTS: ANGELICA DAHURICA ROOT  0.022 mL/100 mL
INACTIVE INGREDIENTS: WATER; CYCLOMETHICONE 5; DIPROPYLENE GLYCOL; CETOSTEARYL ALCOHOL; SHEA BUTTER; BETAINE; CAPRIC ACID; GLYCERYL MONOSTEARATE; 2-ETHYLHEXANOIC ACID; DIMETHICONE; PANTHENOL; STEARIC ACID; Yellow Wax; METHYLPARABEN; TROLAMINE; ETHYLPARABEN; PROPYLPARABEN; ALPHA-TOCOPHEROL ACETATE; DIPROPYLENE GLYCOL; EDETATE TRISODIUM; XANTHAN GUM; CARBOMER 934; PAEONIA LACTIFLORA ROOT; FD&C YELLOW NO. 6; FD&C YELLOW NO. 5

Drug Facts

ACTIVE INGREDIENT

ANGELICA DAHURICA ROOT 0.022mL/100mL

WARNINGS AND PRECAUTIONS

For external use only.

Keep out of reach of children. Is swallowed, get medical help or contact a Poison Control Center right away.

WHEN USING

Keep out of eyes. Rinse with water to remove.

STOP USE

Stop use if a rash or irritation develops and lasts.

PACKAGE LABEL

The History of Whoo
Qi and Jin Eye Cream